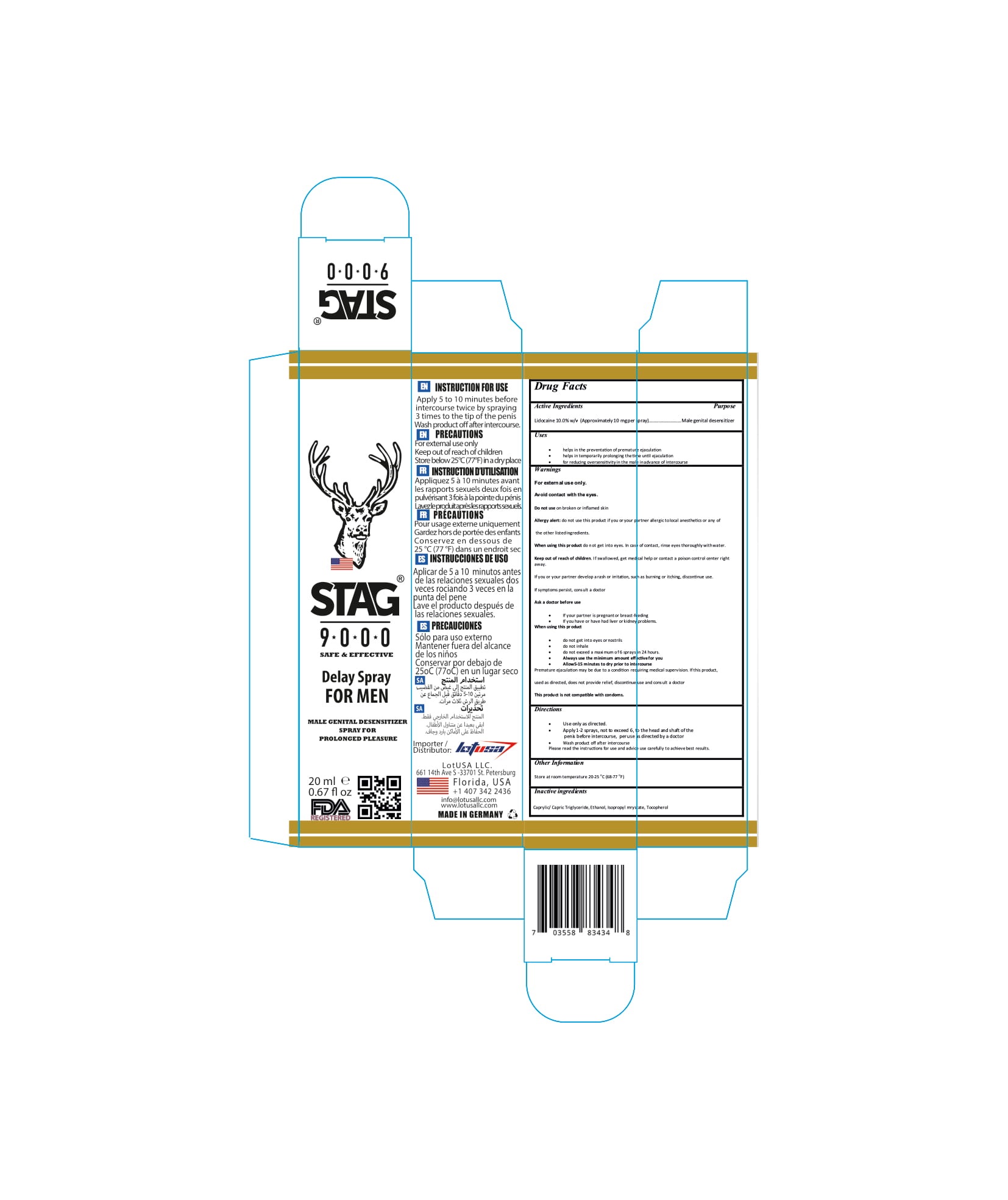 DRUG LABEL: Stag 9000 DelaySpray for men
NDC: 80554-004 | Form: SPRAY
Manufacturer: LOTUSA LLC.
Category: otc | Type: HUMAN OTC DRUG LABEL
Date: 20200923

ACTIVE INGREDIENTS: LIDOCAINE 10 g/100 mL
INACTIVE INGREDIENTS: ISOPROPYL MYRISTATE; TOCOPHEROL; ALCOHOL; MEDIUM-CHAIN TRIGLYCERIDES

STAG 9000 DELAY SPRAY FOR MEN

1. Lidocaine 10.0% w/v (Approximately10 mgper spray)
2. Caprylic/ Capric Triglyceride,
3. Ethanol,
4. Isopropyl mrystate,
5. Tocopherol

The firm does not add other active or inactive ingredients. Different or additional ingredients may impact the quality and potency of the product.

Active Ingredient(s)

Lidocaine 10.0% w/v (Approximately10 mgper spray) Purpose: Male genital desensitizer

Purpose

Male genital desensitizer

Use

• helps in the preventation of premature ejaculation

• helps in temporarily prolonging thetime until ejaculation

• for reducing oversensitivity in the male inadvance of intercourse

Warnings

For external use only. Avoid contact with the eyes.

Do not use

- on broken or inflamed skin

When using this product do not get into eyes. In case of contact, rinse eyes thoroughly withwater.
Keep out of reach of children. If swallowed, get medical help or contact a Poison Control Center right away.

If you or your partner develop a rash or irritation, such as burning or itching, discontinue use. Ifsymptoms persist, consult a doctor Ask a doctor before use

If your partner is pregnant or breast-feeding

If you have or have had liver or kidney problems. When using this pr oduct

do not get into eyes or nostrils

do not inhale

do not exceed a maximum of 6 sprays in 24 hours.

Always use the minimum amount effectivefor you

Allow5-15 minutes to dry prior to intercourse Premature ejaculation may be due to a condition requiring medical supervision. If this product, used as directed, does not provide relief, discontinue use and consult a doctor This product is not compatible with condoms.

Stop use and ask a doctor if irritation or rash occurs. These may be signs of a serious condition.

Keep out of reach of children. If swallowed, get medical help or contact a Poison Control Center right away.

Directions

- • Use only as directed.
- • Apply1-2 sprays, not to exceed 6, to the head and shaft ofthe penis before intercourse, peruse as directed by a doctor
- • Wash product off after intercourse Please read the instructions for use and advice use carefully to achievebest results

Other information

- Store atroom temperature 20-25 o C (68-77 o F)

Inactive ingredients

Caprylic/ Capric Triglyceride, Ethanol, Isopropyl mrystate, Tocopherol

Package Label - Principal Display Panel

20 mL NDC: 80554-004-02